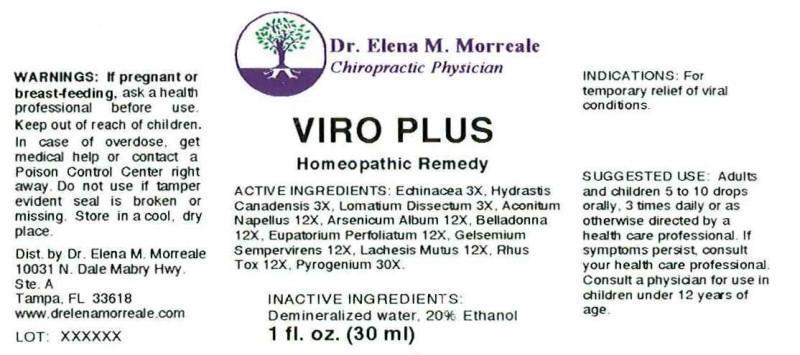 DRUG LABEL: VIRO PLUS
NDC: 50813-0009 | Form: LIQUID
Manufacturer: Dr  Elena M Morreale
Category: homeopathic | Type: HUMAN OTC DRUG LABEL
Date: 20140902

ACTIVE INGREDIENTS: ECHINACEA ANGUSTIFOLIA 3 [hp_X]/1 mL; GOLDENSEAL 3 [hp_X]/1 mL; LOMATIUM DISSECTUM ROOT 3 [hp_X]/1 mL; ACONITUM NAPELLUS 12 [hp_X]/1 mL; ARSENIC TRIOXIDE 12 [hp_X]/1 mL; ATROPA BELLADONNA 12 [hp_X]/1 mL; EUPATORIUM PERFOLIATUM FLOWERING TOP 12 [hp_X]/1 mL; GELSEMIUM SEMPERVIRENS ROOT 12 [hp_X]/1 mL; LACHESIS MUTA VENOM 12 [hp_X]/1 mL; TOXICODENDRON PUBESCENS LEAF 12 [hp_X]/1 mL; RANCID BEEF 30 [hp_X]/1 mL
INACTIVE INGREDIENTS: WATER; ALCOHOL

DRUG FACTS

ACTIVE INGREDIENTS:

Echinacea (Angustifolia) 3X, Hydrastis Canadensis 3X, Lomatium Dissectum 3X, Aconitum Napellus 12X, Arsenicum Album 12X, Belladonna 12X, Eupatorium Perfoliatum 12X, Gelsemium Sempervirens 12X, Lachis Mutus 12X, Rhus Tox 12X, Pyrogenium 30X

INDICATIONS:

For temporary relief of viral conditions.

WARNINGS:

If pregnant or breast-feeding, ask a health care professional before use.

Keep out of reach of children. In case of overdose, get medical help or contact a Poison Control Center right away.

Do not use if tamper evident seal is broken or missing.

Store in cool, dry place.

Keep out of reach of children. In case of overdose, get medical help or contact a Poison Control Center right away.

SUGGESTED USE:

Adults and children 5 to 10 drops orally, 3 times daily or as otherwise directed by a health care professional. If symptoms persist, consult your health care professional. Consult a physician for use in children under 12 years of age.

INDICATIONS:

For temporary relief of viral conditions.

INACTIVE INGREDIENTS:

Demineralized water, 20% Ethanol.

QUESTIONS:

Dist. by Dr. Elena M. Morreale

10031 N Dale Mabry Hwy.

Ste A

Tampa, Fl 33618

www.drelenamorreale.com

PACKAGE LABEL DISPLAY

Dr. Elena M. Morreale

Chiropractic Physician

VIRO PLUS

Homeopathic Remedy

1 fl. oz. (30 ml)